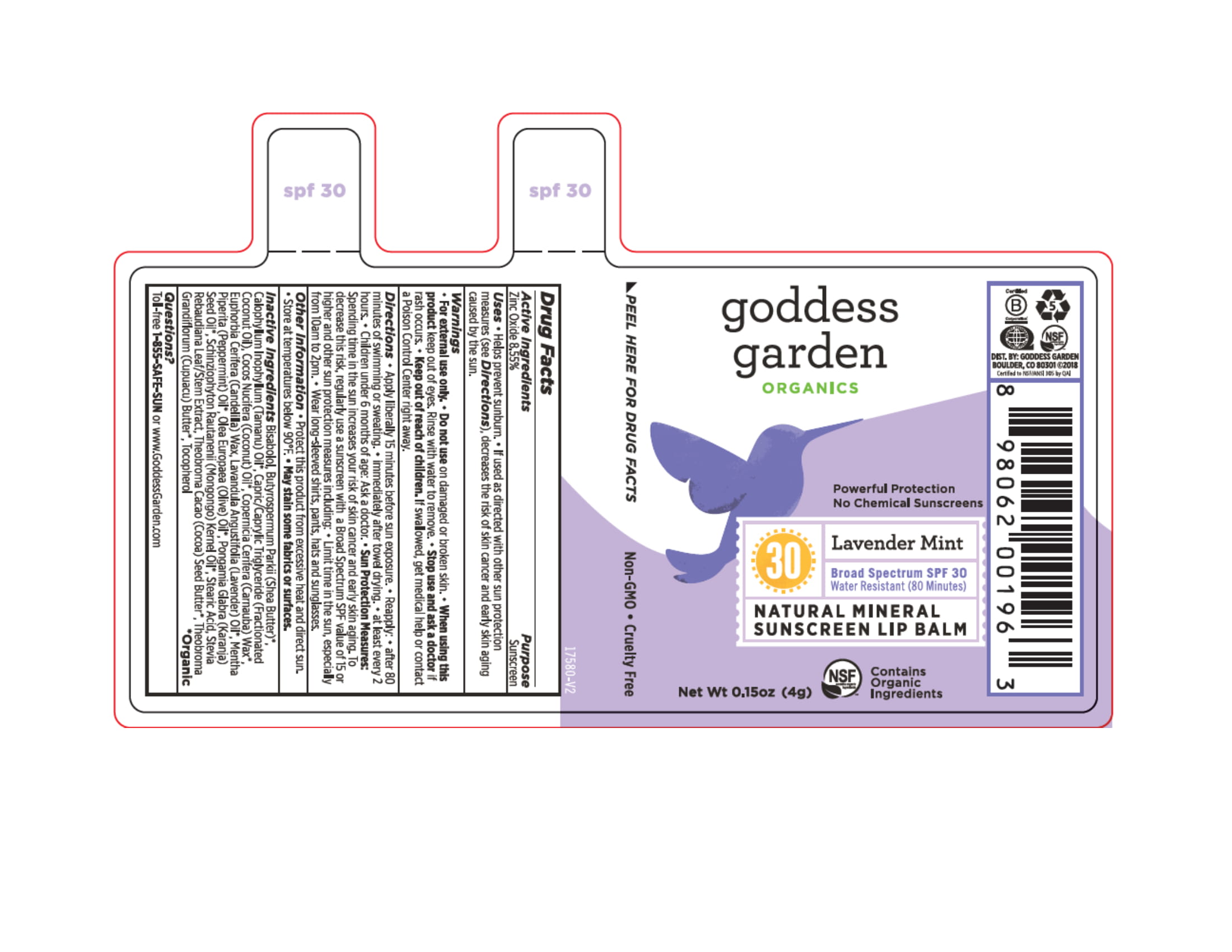 DRUG LABEL: Lip Lavender Mint
NDC: 58479-580 | Form: STICK
Manufacturer: Crossing Cultures LLC dba Goddess Garden
Category: otc | Type: HUMAN OTC DRUG LABEL
Date: 20180522

ACTIVE INGREDIENTS: ZINC OXIDE 8.55 g/100 g
INACTIVE INGREDIENTS: LEVOMENOL; SHEA BUTTER; MEDIUM-CHAIN TRIGLYCERIDES; COCONUT OIL; CANDELILLA WAX; OLIVE OIL; STEVIA REBAUDIUNA LEAF; TOCOPHEROL; KARUM SEED OIL; CARNAUBA WAX; LAVENDER OIL; COCOA BUTTER; TAMANU OIL; STEARIC ACID; MENTHA PIPERITA LEAF; SCHINZIOPHYTON RAUTANENII SEED OIL; THEOBROMA GRANDIFLORUM SEED BUTTER

Goddess Garden Lavender Mint SPF30 Lip Balm

Active Ingredient

Zinc Oxide 8.55%

Purpose

Sunscreen

Uses

* Helps prevent sunburn.

* If used as directed with other sun protection measures (see Directions) decreases the risk of skin cancer and early skin aging caused by the sun.

Warnings

* For external use only.

* Do not use on damaged or broken skin.

* When using this product keep out of eyes. Rinse with water to remove.

* Stop use and ask a doctor if rash occurs.

* Keep out of reach of children. If swallowed, get medical help or contact a Poison Control Center right away.

Do not use

on damaged or broken skin

Stop use and ask doctor

if rash occurs

When using this product

keep out of eyes, rinse with water to remove

Keep out of reach of children

If swallowed, get medical help or contact Pioson Center right away.

Directions

* Apply liberally 15 minutes before sun exposure.

* Reapply:

- After 80 minutes of swimming or sweating.

- Immediately after towel drying.

- At least every 2 hours.

* Children under 6 months of age: Ask a doctor.

* Sun Protection Measures: Spending time in the sun increases your risk of skin cancer and early skin aging. To decrease this risk, regularly use a sunscreen with a Broad Spectrum SPF value of 15 or higher and other sun protection measures including:

- Limit time in sun, especially from 10a.m. to 2p.m.

- Wear long-sleeved shirts, pants, hats and sunglasses.

Other Information

* Protect this product from excessive heat and direct sun.

* Store at temperatures below 90'F.

* May Stain some fabrics or surfaces.

Inactive Ingredients

Bisabolol, Butyrospermum Parkii (Shea Butter)*, Calophyllum Inophyllum (Tamanu) Oil*, Capric/Caprylic Triglyceride (Fractionated Coconut Oil), Cocos Nucifera (Coconut) Oil*, Copernicia Cerifera (Carnauba) Wax*, Euphorbia Cerifera (Candelilla) Wax, Lavandula Angustifolia (Lavender) Oil*, Mentha Piperita (Peppermint) Oil*, Olea Europaea (Olive) Oil*, Pongamia Glabra (Karanja) Seed Oil*, Schinziophyton Rautanenii (Mongongo) Kernel Oil*, Stearic Acid, Stevia Rebaudiana Leaf/Stem Extract, Theobroma Cacao (Cocoa) Seed Butter*, Theobroma Grandiflorum (Cupuacu) Butter*, Tocopherol

*Organic

Questions or Comments

Toll-free 1-855-SAFE-SUN or www.GoddessGarden.com